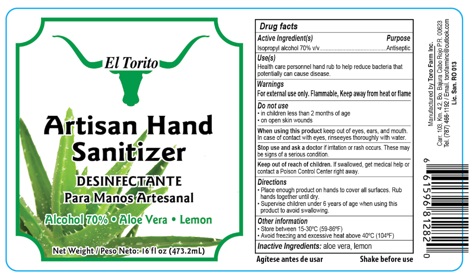 DRUG LABEL: Artisan Hand Sanitizer
NDC: 80842-001 | Form: GEL
Manufacturer: Toro Farm Inc.
Category: otc | Type: HUMAN OTC DRUG LABEL
Date: 20210108

ACTIVE INGREDIENTS: ISOPROPYL ALCOHOL 0.7 mL/1 mL
INACTIVE INGREDIENTS: ALOE VERA LEAF; LEMON

Artisan Hand Sanitizer

Active ingredient(s)

Isopropyl alcohol 70% v/v

Purpose

Antiseptic

Use[s]

Health care personnel hard to help reduce bacteria that potentially can cause disease.

Warnings

For external use only. Flammable. Keep away from heat or flame

Do not use

• in children less than 2 months of age

• on open skin wounds

When using this product

keep out of eyes, ears, and mouth. In case of contact with eyes, rinseeyes thoroughly with water.

Stop use and ask a doctor

if irritation or rash occurs. These may be signs of a serious condition.

Keep out of reach of children.

If swallowed, get medical help or contact a Poison Control Center right away.

Directions

- Place enough product on hands to cover all surfaces. Rub hands together until dry.
- Supervise children under 6 years of age when using this product to avoid swallowing.

Other information

- Store between 15-30°C (59-86°F)
- Avoid freezing and excessive heat above 40°C (104°F)

Inactive ingredients:

aloe vera, lemon